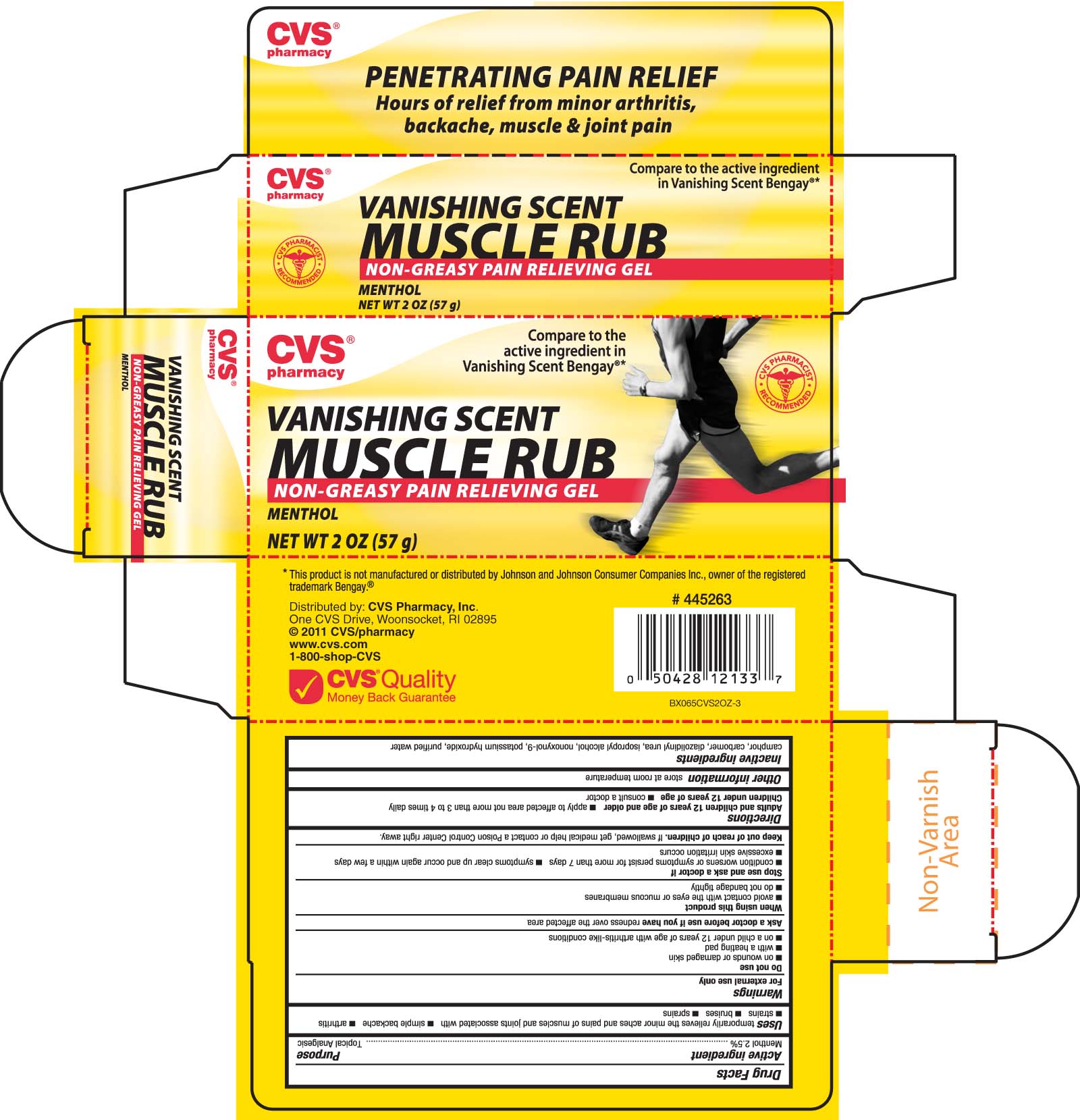 DRUG LABEL: CVS Vanishing Scent Muscle Rub
NDC: 59779-054 | Form: GEL
Manufacturer: CVS Pharmacy
Category: otc | Type: HUMAN OTC DRUG LABEL
Date: 20110314

ACTIVE INGREDIENTS: MENTHOL 27.5 mg/1 g
INACTIVE INGREDIENTS: WATER; CARBOMER 934; DIAZOLIDINYL UREA; ISOPROPYL ALCOHOL; CAMPHOR (SYNTHETIC); NONOXYNOL-9; POTASSIUM HYDROXIDE

DRUG FACTS

Active ingredient Purpose
Menthol 2.5%.................................................Topical Analgesic

PURPOSE

Uses temporarily relieves the minor aches and pains of muscles and joints associated with
- simple backache - atrhritis - strains - bruises - sprains

Keep out of reach of children. If swallowed, get medical help or contact a
Poison Control Center right away.

INDICATIONS AND USAGE

Uses temporarily relieves the minor aches and pains of muscles and joints associated with
- simple backache - atrhritis - strains - bruises - sprains

Warnings
For external use only
Do not use
- on wounds or damaged skin
- with a heating pad
- on a child under 12 years of age with arthritis-like conditions
Ask a doctor before use if you have redness over the affected area.
When using this product
- avoid contact with the eyes or mucous membranes
- do not bandage tightly
Stop use and ask a doctor if
- condition worsens or symptoms persist for more than 7 days
- symptoms clear up and occur again within a few days
- excessive skin irritation occurs.
Keep out of reach of children. If swallowed, get medical help or contact a Poison
Control Center right away.

Directions
Adults and children 12 years of age and older - apply to the affected area not more than 3 to 4
times daily.
Children under 12 years of age - consult a doctor

Inactive Ingredients
camphor, carbomer, diazolidinyl urea, isopropyl alcohol, nonoxynol-9, potassium hydroxide, purified water